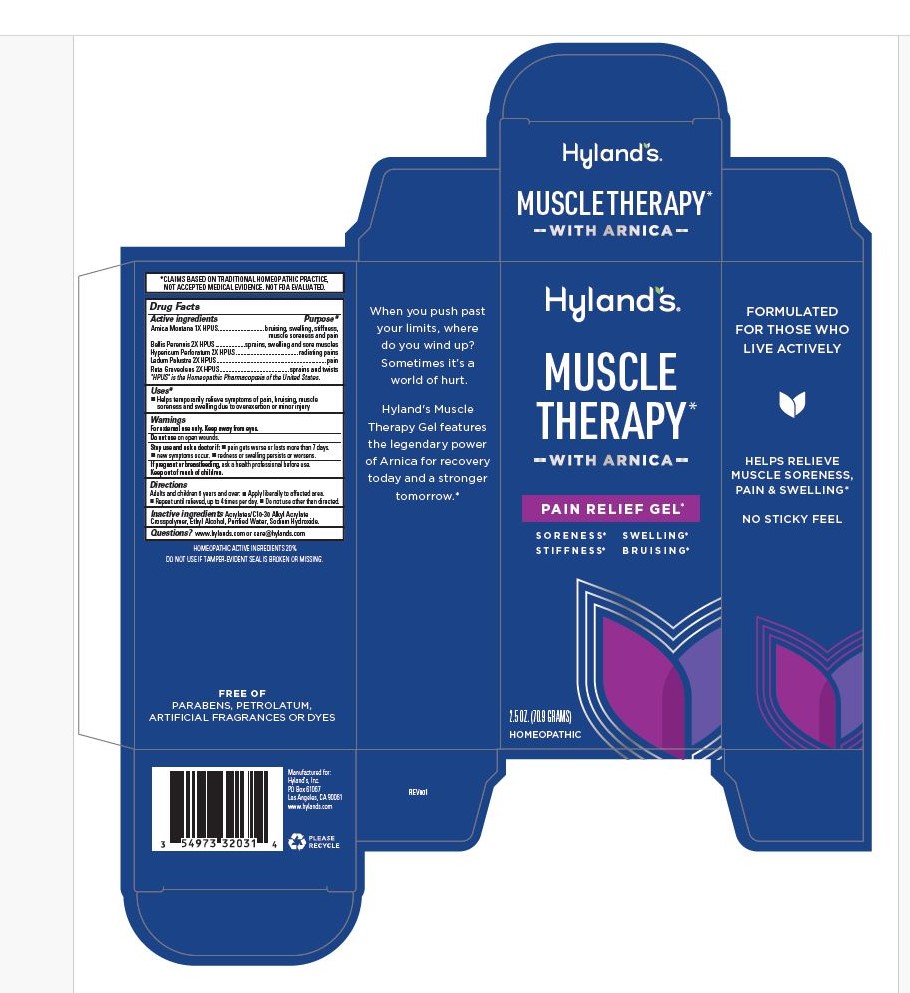 DRUG LABEL: Muscle Therapy with Arnica Pain Relief Gel
NDC: 54973-3203 | Form: GEL
Manufacturer: Hyland’s Inc.
Category: homeopathic | Type: HUMAN OTC DRUG LABEL
Date: 20240925

ACTIVE INGREDIENTS: ARNICA MONTANA 1 [hp_X]/1 g; BELLIS PERENNIS 2 [hp_X]/1 g; HYPERICUM PERFORATUM 2 [hp_X]/1 g; RUTA GRAVEOLENS FLOWERING TOP 2 [hp_X]/1 g; RHODODENDRON TOMENTOSUM LEAFY TWIG 2 [hp_X]/1 g
INACTIVE INGREDIENTS: ALCOHOL; WATER; SODIUM HYDROXIDE

Hyland's Muscle Therapy with Arnica Pain Relief Gel

Purpose

Temporarily relieves symptoms of pain, bruising, muscle soreness and
swelling due to overexertion or injury.

Drug Facts

Active ingredients

Active ingredients | Purpose
Arnica Montana 1X HPUS | bruising, swelling, stiffness, muscle soreness and pain
Bellis Perennis 2X HPUS | sprains, swelling and sore muscles
Hypericum Perforatum 2X HPUS | radiating pains
Ledum Palustre 2X HPUS | pain
Ruta Graveolens 2X HPUS | sprains and twist

"HPUS" is the Homeopathic Pharmacopoeia of the United States.

Uses

Temporarily relieves the symptoms of pain, bruising, muscle soreness and swelling due to overexertion or injury.

Warnings

For external use only. Keep away from eyes.

Do not use

on open wounds.

Stop use and ask a doctor if

■ pain gets worse or lasts more than 7 days.
■ new symptoms occur. ■ redness or swelling persists or worsens.

If pregnant or breastfeeding

ask a health professional before use.

Directions

Adults and children 6 years and over: ■ Apply liberally to affected area. ■ Repeat until relieved, up to 4 times per day. ■ Do not use other than directed.

Inactive ingredients

Carbopol ® Ultrez 21 Polymer, Ethyl Alcohol, Purified Water, Sodium Hydroxide

Questions?

www.hylands.com or (800) 624-9659

Dosage and Administration (Directions)

Adults and children 6 years and over:  Apply liberally to affected area.
 Repeat until relieved, up to 4 times per day.  Do not use other than directed.

Principal Display Panel - 70.9 Grams Gel Tube Carton

Hyland's

NATURALS™

MUSCLE

THERAPY

-WITH ARNICA-

PAIN RELIEF GEL*

SORENESS SWELLING

STIFFNESS BRUISING

HOMEOPATHIC

2.5 OZ. (70.9 GRAMS)